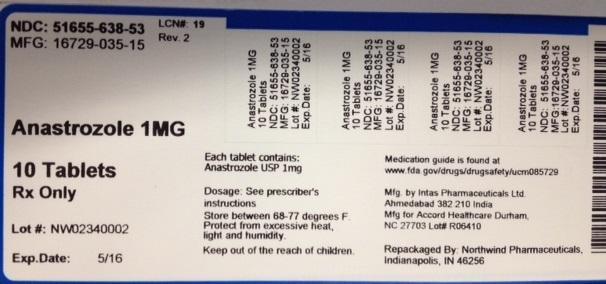 DRUG LABEL: Anastrozole
NDC: 51655-638 | Form: TABLET
Manufacturer: Northwind Pharmaceuticals, LLC
Category: prescription | Type: HUMAN PRESCRIPTION DRUG LABEL
Date: 20141110

ACTIVE INGREDIENTS: ANASTROZOLE 1 mg/1 1

Anastrozole

INDICATIONS & USAGE

1.1 Adjuvant Treatment

Anastrozole tablets are indicated for adjuvant treatment of postmenopausal women with hormone receptor-positive early breast cancer.

1.2 First-Line Treatment

Anastrozole tablets are indicated for the first-line treatment of postmenopausal women with hormone receptor-positive or hormone receptor unknown locally advanced or metastatic breast cancer.

1.3 Second-Line Treatment

Anastrozole tablets are indicated for the treatment of advanced breast cancer in postmenopausal women with disease progression following tamoxifen therapy. Patients with ER-negative disease and patients who did not respond to previous tamoxifen therapy rarely responded to anastrozole tablets.

DOSAGE & ADMINISTRATION

2.1 Recommended Dose

The dose of anastrozole tablet is one 1 mg tablet taken once a day. For patients with advanced breast cancer, anastrozole tablets should be continued until tumor progression. Anastrozole tablets can be taken with or without food.

For adjuvant treatment of early breast cancer in postmenopausal women, the optimal duration of therapy is unknown. In the ATAC trial, anastrozole was administered for five years [see Clinical Studies (14.1)].

No dosage adjustment is necessary for patients with renal impairment or for elderly patients [see Use in Specific Populations (8.6)].

2.2 Patients with Hepatic Impairment

No changes in dose are recommended for patients with mild-to-moderate hepatic impairment. Anastrozole has not been studied in patients with severe hepatic impairment [see Use in Specific Populations (8.7)].

DOSAGE FORMS & STRENGTHS

The tablets are white to off-white, round biconvex, film coated tablets, with “AHI” debossing on one side and plain on other side.

CONTRAINDICATIONS

4.1 Pregnancy and Premenopausal Women

Anastrozole may cause fetal harm when administered to a pregnant woman and offers no clinical benefit to premenopausal women with breast cancer. Anastrozole is contraindicated in women who are or may become pregnant. There are no adequate and well-controlled studies in pregnant women using anastrozole. If anastrozole is used during pregnancy, or if the patient becomes pregnant while taking this drug, the patient should be apprised of the potential hazard to a fetus or potential risk for loss of the pregnancy [see Use in Specific Populations (8.1)].

4.2 Hypersensitivity

Anastrozole is contraindicated in any patient who has shown a hypersensitivity reaction to the drug or to any of the excipients. Observed reactions include anaphylaxis, angioedema, and urticaria [see Adverse Reactions (6.2)].

WARNINGS AND PRECAUTIONS

5.1 Ischemic Cardiovascular Events

In women with pre-existing ischemic heart disease, an increased incidence of ischemic cardiovascular events was observed with anastrozole in the ATAC trial (17% of patients on anastrozole and 10% of patients on tamoxifen). Consider risk and benefits of anastrozole therapy in patients with pre-existing ischemic heart disease [see Adverse Reactions (6.1)].

5.2 Bone Effects

Results from the ATAC trial bone substudy at 12 and 24 months demonstrated that patients receiving anastrozole had a mean decrease in both lumbar spine and total hip bone mineral density (BMD) compared to baseline. Patients receiving tamoxifen had a mean increase in both lumbar spine and total hip BMD compared to baseline. Consider bone mineral density monitoring in patients treated with anastrozole [see Adverse Reactions (6.1)] .

5.3 Cholesterol

During the ATAC trial, more patients receiving anastrozole were reported to have elevated serum cholesterol compared to patients receiving tamoxifen (9% versus 3.5%, respectively) [see Adverse Reactions (6.1)].

ADVERSE REACTIONS

Serious adverse reactions with anastrozole occurring in less than 1 in 10,000 patients, are: 1) skin reactions such as lesions, ulcers, or blisters; 2) allergic reactions with swelling of the face, lips, tongue, and/or throat. This may cause difficulty in swallowing and/or breathing; and 3) changes in blood tests of the liver function, including inflammation of the liver with symptoms that may include a general feeling of not being well, with or without jaundice, liver pain or liver swelling [see Adverse Reactions (6.2)].

Common adverse reactions (occurring with an incidence of ≥10%) in women taking anastrozole included: hot flashes, asthenia, arthritis, pain, arthralgia, hypertension, depression, nausea and vomiting, rash, osteoporosis, fractures, back pain, insomnia, headache, bone pain, peripheral edema, increased cough, dyspnea, pharyngitis and lymphedema.

In the ATAC trial, the most common reported adverse reaction (>0.1%) leading to discontinuation of therapy for both treatment groups was hot flashes, although there were fewer patients who discontinued therapy as a result of hot flashes in the anastrozole group.

Because clinical trials are conducted under widely varying conditions, adverse reaction rates observed in the clinical trials of a drug cannot be directly compared to rates in the clinical trials of another drug and may not reflect the rates observed in practice.

6.1 Clinical Trials Experience

Adjuvant Therapy

Adverse reaction data for adjuvant therapy are based on the ATAC trial [see Clinical Studies (14.1)]. The median duration of adjuvant treatment for safety evaluation was 59.8 months and 59.6 months for patients receiving anastrozole 1 mg and tamoxifen 20 mg, respectively. For the list of adverse events please see the manufacturer's drug information.

PLEASE REVIEW THE MANUFACTURER'S COMPLETE DRUG INFORMATION AT THE FDA SITE:

http://dailymed.nlm.nih.gov/dailymed/drugInfo.cfm?setid=03586c40-eb32-45c5-beb7-6762a6b78790

Ischemic Cardiovascular Events

Between treatment arms in the overall population of 6186 patients, there was no statistical difference in ischemic cardiovascular events (4% anastrozole vs. 3% tamoxifen). In the overall population, angina pectoris was reported in 71/3092 (2.3%) patients in the anastrozole arm and 51/3094 (1.6%) patients in the tamoxifen arm; myocardial infarction was reported in 37/3092 (1.2%) patients in the anastrozole arm and 34/3094 (1.1%) patients in the tamoxifen arm.

In women with pre-existing ischemic heart disease 465/6186 (7.5%), the incidence of ischemic cardiovascular events was 17% in patients on anastrozole and 10% in patients on tamoxifen. In this patient population, angina pectoris was reported in 25/216 (11.6%) patients receiving anastrozole and 13/249 (5.2%) patients receiving tamoxifen; myocardial infarction was reported in 2/216 (0.9%) patients receiving anastrozole and 8/249 (3.2%) patients receiving tamoxifen.

Bone Mineral Density Findings

Results from the ATAC trial bone substudy at 12 and 24 months demonstrated that patients receiving anastrozole had a mean decrease in both lumbar spine and total hip bone mineral density (BMD) compared to baseline. Patients receiving tamoxifen had a mean increase in both lumbar spine and total hip BMD compared to baseline.

Because anastrozole lowers circulating estrogen levels it may cause a reduction in bone mineral density.

A post-marketing trial assessed the combined effects of anastrozole and the bisphosphonate risedronate on changes from baseline in BMD and markers of bone resorption and formation in postmenopausal women with hormone receptor-positive early breast cancer. All patients received calcium and vitamin D supplementation. At 12 months, small reductions in lumbar spine bone mineral density were noted in patients not receiving bisphosphonates. Bisphosphonate treatment preserved bone density in most patients at risk of fracture.

Postmenopausal women with early breast cancer scheduled to be treated with anastrozole should have their bone status managed according to treatment guidelines already available for postmenopausal women at similar risk of fragility fracture.

Cholesterol

During the ATAC trial, more patients receiving anastrozole were reported to have an elevated serum cholesterol compared to patients receiving tamoxifen (9% versus 3.5%, respectively).

A post-marketing trial also evaluated any potential effects of anastrozole on lipid profile. In the primary analysis population for lipids (anastrozole alone), there was no clinically significant change in LDL-C from baseline to 12 months and HDL-C from baseline to 12 months.

In secondary population for lipids (anastrozole+risedronate), there also was no clinically significant change in LDL-C and HDL-C from baseline to 12 months.

In both populations for lipids, there was no clinically significant difference in total cholesterol (TC) or serum triglycerides (TG) at 12 months compared with baseline.

In this trial, treatment for 12 months with anastrozole alone had a neutral effect on lipid profile. Combination treatment with anastrozole and risedronate also had a neutral effect on lipid profile.

The trial provides evidence that postmenopausal women with early breast cancer scheduled to be treated with anastrozole should be managed using the current National Cholesterol Education Program guidelines for cardiovascular risk-based management of individual patients with LDL elevations.

Other Adverse Reactions

Patients receiving anastrozole had an increase in joint disorders (including arthritis, arthrosis and arthralgia) compared with patients receiving tamoxifen. Patients receiving anastrozole had an increase in the incidence of all fractures (specifically fractures of spine, hip and wrist) [315 (10%)] compared with patients receiving tamoxifen [209 (7%)].

Patients receiving anastrozole had a higher incidence of carpal tunnel syndrome [78 (2.5%)] compared with patients receiving tamoxifen [22 (0.7%)].

Vaginal bleeding occurred more frequently in the tamoxifen-treated patients versus the anastrozole -treated patients 317 (10%) versus 167 (5%), respectively.

Patients receiving anastrozole had a lower incidence of hot flashes, vaginal bleeding, vaginal discharge, endometrial cancer, venous thromboembolic events and ischemic cerebrovascular events compared with patients receiving tamoxifen.

10-year median follow-up Safety Results from the ATAC Trial

Results are consistent with the previous analyses.
Serious adverse reactions were similar between anastrozole (50%) and tamoxifen (51%).
Cardiovascular events were consistent with the known safety profiles of anastrozole and tamoxifen.
The cumulative incidences of all first fractures (both serious and non-serious, occurring either during or after treatment) was higher in the anastrozole group (15%) compared to the tamoxifen group (11%). This increased first fracture rate during treatment did not continue in the post-treatment follow-up period.
The cumulative incidence of new primary cancers was similar in the anastrozole group (13.7%) compared to the tamoxifen group (13.9%). Consistent with the previous analyses, endometrial cancer was higher in the tamoxifen group (0.8%) compared to the anastrozole group (0.2%).
The overall number of deaths (during or off-trial treatment) was similar between the treatment groups. There were more deaths related to breast cancer in the tamoxifen than in the anastrozole treatment group.

PLEASE REVIEW THE MANUFACTURER'S COMPLETE DRUG INFORMATION THAT INCLUDES FIRST-LINE THERAPY, SECOND-LINE THERAPY AND ALL OTHER IMPORTANT INFORMATION AT THE FDA SITE:

http://dailymed.nlm.nih.gov/dailymed/drugInfo.cfm?setid=03586c40-eb32-45c5-beb7-6762a6b78790

6.2 Post-Marketing Experience

These adverse reactions are reported voluntarily from a population of uncertain size. Therefore, it is not always possible to estimate reliably their frequency or establish a causal relationship to drug exposure. The following have been reported in post-approval use of anastrozole:

Hepatobiliary events including increases in alkaline phosphatase, alanine aminotransferase, aspartate aminotransferase, gamma-GT, and bilirubin; hepatitis

Rash including cases of mucocutaneous disorders such as erythema multiforme and Stevens-Johnson syndrome.

Cases of allergic reactions including angioedema, urticaria and anaphylaxis. [see Contraindications (4.2)]

Myalgia, trigger finger and hypercalcemia (with or without an increase in parathyroid hormone)

DRUG INTERACTIONS

7.1 Tamoxifen

Co-administration of anastrozole and tamoxifen in breast cancer patients reduced anastrozole plasma concentration by 27%. However, the co-administration of anastrozole and tamoxifen did not affect the pharmacokinetics of tamoxifen or N-desmethyltamoxifen. At a median follow-up of 33 months, the combination of anastrozole and tamoxifen did not demonstrate any efficacy benefit when compared with tamoxifen in all patients as well as in the hormone receptor-positive subpopulation. This treatment arm was discontinued from the trial. [see Clinical Studies (14.1)] . Based on clinical and pharmacokinetic results from the ATAC trial, tamoxifen should not be administered with anastrozole.

7.2 Estrogen

Estrogen-containing therapies should not be used with anastrozole as they may diminish its pharmacological action.

7.3 Warfarin

In a study conducted in 16 male volunteers, anastrozole did not alter the exposure (as measured by C max and AUC), and anticoagulant activity (as measured by prothrombin time, activated partial thromboplastin time, and thrombin time) of both R- and S-warfarin.

7.4 Cytochrome P450

Based on in vitro and in vivo results, it is unlikely that co-administration of anastrozole 1 mg will affect other drugs as a result of inhibition of cytochrome P450 [see Clinical Pharmacology (12.3)].

USE IN SPECIFIC POPULATIONS

8.1 Pregnancy

PREGNANCY CATEGORY X [see Contraindications (4.1)]

Anastrozole may cause fetal harm when administered to a pregnant woman and offers no clinical benefit to premenopausal women with breast cancer. Anastrozole is contraindicated in women who are or may become pregnant. In animal studies, anastrozole caused pregnancy failure, increased pregnancy loss, and signs of delayed fetal development. There are no studies of anastrozole use in pregnant women. If anastrozole is used during pregnancy, or if the patient becomes pregnant while receiving this drug, the patient should be apprised of the potential hazard to the fetus and potential risk for pregnancy loss.

In animal reproduction studies, pregnant rats and rabbits received anastrozole during organogenesis at doses equal to or greater than 1 (rats) and 1/3 (rabbits) the recommended human dose on a mg/m 2 basis. In both species, anastrozole crossed the placenta, and there was increased pregnancy loss (increased pre- and/or post-implantation loss, increased resorption, and decreased numbers of live fetuses). In rats, these effects were dose related, and placental weights were significantly increased. Fetotoxicity, including delayed fetal development (i.e., incomplete ossification and depressed fetal body weights), occurred in rats at anastrozole doses that produced peak plasma levels 19 times higher than serum levels in humans at the therapeutic dose (AUC 0-24hr 9 times higher). In rabbits, anastrozole caused pregnancy failure at doses equal to or greater than 16 times the recommended human dose on a mg/m 2 basis [see Animal Toxicology and/or Pharmacology (13.2)].

8.3 Nursing Mothers

It is not known if anastrozole is excreted in human milk. Because many drugs are excreted in human milk and because of the tumorigenicity shown for anastrozole in animal studies, or the potential for serious adverse reactions in nursing infants, a decision should be made whether to discontinue nursing or to discontinue the drug, taking into account the importance of the drug to the mother.

8.4 Pediatric Use

Clinical studies in pediatric patients included a placebo-controlled trial in pubertal boys of adolescent age with gynecomastia and a single-arm trial in girls with McCune-Albright Syndrome and progressive precocious puberty. The efficacy of anastrozole in the treatment of pubertal gynecomastia in adolescent boys and in the treatment of precocious puberty in girls with McCune-Albright Syndrome has not been demonstrated.

Gynecomastia Study

A randomized, double-blind, placebo-controlled, multi-center study enrolled 80 boys with pubertal gynecomastia aged 11 to 18 years. Patients were randomized to a daily regimen of either anastrozole 1 mg or placebo. After 6 months of treatment there was no statistically significant difference in the percentage of patients who experienced a ≥50% reduction in gynecomastia (primary efficacy analysis). Secondary efficacy analyses (absolute change in breast volume, the percentage of patients who had any reduction in the calculated volume of gynecomastia, breast pain resolution) were consistent with the primary efficacy analysis. Serum estradiol concentrations at Month 6 of treatment were reduced by 15.4% in the anastrozole group and 4.5% in the placebo group.

Adverse reactions that were assessed as treatment-related by the investigators occurred in 16.3% of the anastrozole-treated patients and 8.1% of the placebo-treated patients with the most frequent being acne (7% anastrozole and 2.7% placebo) and headache (7% anastrozole and 0% placebo); all other adverse reactions showed small differences between treatment groups. One patient treated with anastrozole discontinued the trial because of testicular enlargement. The mean baseline-subtracted change in testicular volume after 6 months of treatment was + 6.6 ± 7.9 cm 3 in the anastrozole-treated patients and + 5.2 ± 8.0 cm 3 in the placebo group.

McCune-Albright Syndrome Study

A multi-center, single-arm, open-label study was conducted in 28 girls with McCune-Albright Syndrome and progressive precocious puberty aged 2 to <10 years. All patients received a 1 mg daily dose of anastrozole. The trial duration was 12 months. Patients were enrolled on the basis of a diagnosis of typical (27/28) or atypical (1/27) McCune-Albright Syndrome, precocious puberty, history of vaginal bleeding, and/or advanced bone age. Patients’ baseline characteristics included the following: a mean chronological age of 5.9 ± 2.0 years, a mean bone age of 8.6 ± 2.6 years, a mean growth rate of 7.9 ± 2.9 cm/year and a mean Tanner stage for breast of 2.7 ± 0.81. Compared to pre-treatment data there were no on-treatment statistically significant reductions in the frequency of vaginal bleeding days, or in the rate of increase of bone age (defined as a ratio between the change in bone age over the change of chronological age). There were no clinically significant changes in Tanner staging,mean ovarian volume, mean uterine volume and mean predicted adult height. A small but statistically significant reduction of growth rate from 7.9 ± 2.9 cm/year to 6.5 ± 2.8 cm/year was observed but the absence of a control group precludes attribution of this effect to treatment or to other confounding factors such as variations in endogenous estrogen levels commonly seen in McCune-Albright Syndrome patients.

Five patients (18%) experienced adverse reactions that were considered possibly related to anastrozole. These were nausea, acne, pain in an extremity, increased alanine transaminase and aspartate transaminase, and allergic dermatitis.

Pharmacokinetics in Pediatric Patients

Following 1 mg once daily multiple administration in pediatric patients, the mean time to reach the maximum anastrozole concentration was 1 hr. The mean (range) disposition parameters of anastrozole in pediatric patients were described by a CL/F of 1.54 L/h (0.77 to 4.53 L/h) and V/F of 98.4 L (50.7 to 330.0 L). The terminal elimination half-life was 46.8 h, which was similar to that observed in postmenopausal women treated with anastrozole for breast cancer. Based on a population pharmacokinetic analysis, the pharmacokinetics of anastrozole was similar in boys with pubertal gynecomastia and girls with McCune- Albright Syndrome.

8.5 Geriatric Use

In studies 0030 and 0027, about 50% of patients were 65 or older. Patients ≥ 65 years of age had moderately better tumor response and time to tumor progression than patients < 65 years of age regardless of randomized treatment. In studies 0004 and 0005, 50% of patients were 65 or older. Response rates and time to progression were similar for the over 65 and younger patients.

In the ATAC study, 45% of patients were 65 years of age or older. The efficacy of anastrozole compared to tamoxifen in patients who were 65 years or older (N=1413 for anastrozole and N=1410 for tamoxifen, the hazard ratio for disease-free survival was 0.93 [95% CI: 0.80, 1.08]) was less than efficacy observed in patients who were less than 65 years of age (N=1712 for anastrozole and N=1706 for tamoxifen, the hazard ratio for disease-free survival was 0.79 [95% CI: 0.67, 0.94]).

The pharmacokinetics of anastrozole is not affected by age.

8.6 Renal Impairment

Since only about 10% of anastrozole is excreted unchanged in the urine, the renal impairment does not influence the total body clearance. Dosage adjustment in patients with renal impairment is not necessary [see Dosage and Administration (2.1) and Clinical Pharmacology (12.3)].

8.7 Hepatic Impairment

The plasma anastrozole concentrations in the subjects with hepatic cirrhosis were within the range of concentrations seen in normal subjects across all clinical trials. Therefore, dosage adjustment is also not necessary in patients with stable hepatic cirrhosis. Anastrozole has not been studied in patients with severe hepatic impairment [see Dosage and Administration (2.2) and Clinical Pharmacology (12.3)].

OVERDOSAGE

Clinical trials have been conducted with anastrozole, up to 60 mg in a single dose given to healthy male volunteers and up to 10 mg daily given to postmenopausal women with advanced breast cancer; these dosages were tolerated. A single dose of anastrozole that results in life-threatening symptoms has not been established. There is no specific antidote to overdosage and treatment must be symptomatic. In the management of an overdose, consider that multiple agents may have been taken. Vomiting may be induced if the patient is alert. Dialysis may be helpful because anastrozole is not highly protein bound. General supportive care, including frequent monitoring of vital signs and close observation of the patient, is indicated.

DESCRIPTION

Anastrozole tablets for oral administration contain 1 mg of anastrozole, a non-steroidal aromatase inhibitor. It is chemically described as 1,3-Benzenediacetonitrile, a, a, a', a'-tetramethyl-5-(1H-1,2,4-triazol-1-ylmethyl). Its molecular formula is C 17H 19N 5.

Anastrozole is an off-white powder with a molecular weight of 293.4. Anastrozole has moderate aqueous solubility (0.5 mg/mL at 25°C); solubility is independent of pH in the physiological range. Anastrozole is freely soluble in methanol, acetone, ethanol, and tetrahydrofuran, and very soluble in acetonitrile.

Each tablet contains as inactive ingredients: lactose monohydrate, magnesium stearate, hypromellose, macrogol, povidone, sodium starch glycolate, and titanium dioxide.

CLINICAL PHARMACOLOGY

12.1 Mechanism of Action

The growth of many cancers of the breast is stimulated or maintained by estrogens.

In postmenopausal women, estrogens are mainly derived from the action of the aromatase enzyme, which converts adrenal androgens (primarily androstenedione and testosterone) to estrone and estradiol. The suppression of estrogen biosynthesis in peripheral tissues and in the cancer tissue itself can therefore be achieved by specifically inhibiting the aromatase enzyme.

Anastrozole is a selective non-steroidal aromatase inhibitor. It significantly lowers serum estradiol concentrations and has no detectable effect on formation of adrenal corticosteroids or aldosterone.

12.2 Pharmacodynamics

Effect on Estradiol

Mean serum concentrations of estradiol were evaluated in multiple daily dosing trials with 0.5, 1, 3, 5, and 10 mg of anastrozole in postmenopausal women with advanced breast cancer. Clinically significant suppression of serum estradiol was seen with all doses. Doses of 1 mg and higher resulted in suppression of mean serum concentrations of estradiol to the lower limit of detection (3.7 pmol/L). The recommended daily dose, anastrozole 1 mg, reduced estradiol by approximately 70% within 24 hours and by approximately 80% after 14 days of daily dosing. Suppression of serum estradiol was maintained for up to 6 days after cessation of daily dosing with anastrozole 1 mg.

The effect of anastrozole in premenopausal women with early or advanced breast cancer has not been studied. Because aromatization of adrenal androgens is not a significant source of estradiol in premenopausal women, anastrozole would not be expected to lower estradiol levels in premenopausal women.

Effect on Corticosteroids

In multiple daily dosing trials with 3, 5, and 10 mg, the selectivity of anastrozole was assessed by examining effects on corticosteroid synthesis. For all doses, anastrozole did not affect cortisol or aldosterone secretion at baseline or in response to ACTH. No glucocorticoid or mineralocorticoid replacement therapy is necessary with anastrozole.

Other Endocrine Effects

In multiple daily dosing trials with 5 and 10 mg, thyroid stimulating hormone (TSH) was measured; there was no increase in TSH during the administration of anastrozole. Anastrozole does not possess direct progestogenic, androgenic, or estrogenic activity in animals, but does perturb the circulating levels of progesterone, androgens, and estrogens.

12.3 Pharmacokinetics

Absorption

Inhibition of aromatase activity is primarily due to anastrozole, the parent drug. Absorption of anastrozole is rapid and maximum plasma concentrations typically occur within 2 hours of dosing under fasted conditions. Studies with radiolabeled drug have demonstrated that orally administered anastrozole is well absorbed into the systemic circulation. Food reduces the rate but not the overall extent of anastrozole absorption. The mean C max of anastrozole decreased by 16% and the median T max was delayed from 2 to 5 hours when anastrozole was administered 30 minutes after food. The pharmacokinetics of anastrozole are linear over the dose range of 1 to 20 mg, and do not change with repeated dosing. The pharmacokinetics of anastrozole were similar in patients and healthy volunteers.

Distribution

Steady-state plasma levels are approximately 3- to 4-fold higher than levels observed after a single dose of anastrozole. Plasma concentrations approach steady-state levels at about 7 days of once daily dosing. Anastrozole is 40% bound to plasma proteins in the therapeutic range.

Metabolism

Metabolism of anastrozole occurs by N-dealkylation, hydroxylation and glucuronidation. Three metabolites of anastrozole (triazole, a glucuronide conjugate of hydroxy-anastrozole, and a glucuronide conjugate of anastrozole itself) have been identified in human plasma and urine. The major circulating metabolite of anastrozole, triazole, lacks pharmacologic activity.

Anastrozole inhibited reactions catalyzed by cytochrome P450 1A2, 2C8/9, and 3A4 in vitro with Ki values which were approximately 30 times higher than the mean steady-state Cmax values observed following a 1 mg daily dose. Anastrozole had no inhibitory effect on reactions catalyzed by cytochrome P450 2A6 or 2D6 in vitro. Administration of a single 30 mg/kg or multiple 10 mg/kg doses of anastrozole to healthy subjects had no effect on the clearance of antipyrine or urinary recovery of antipyrine metabolites.

Excretion

Eighty-five percent of radiolabeled anastrozole was recovered in feces and urine. Hepatic metabolism accounts for approximately 85% of anastrozole elimination. Renal elimination accounts for approximately 10% of total clearance. The mean elimination half-life of anastrozole is 50 hours.

Effect of Gender and Age

Anastrozole pharmacokinetics have been investigated in postmenopausal female volunteers and patients with breast cancer. No age-related effects were seen over the range <50 to >80 years.

Effect of Race

Estradiol and estrone sulfate serum levels were similar between Japanese and Caucasian postmenopausal women who received 1 mg of anastrozole daily for 16 days. Anastrozole mean steady-state minimum plasma concentrations in Caucasian and Japanese postmenopausal women were 25.7 and 30.4 ng/mL, respectively.

Effect of Renal Impairment

Anastrozole pharmacokinetics have been investigated in subjects with renal impairment. Anastrozole renal clearance decreased proportionally with creatinine clearance and was approximately 50% lower in volunteers with severe renal impairment (creatinine clearance < 30 mL/min/1.73m2) compared to controls. Total clearance was only reduced 10%. No dosage adjustment is needed for renal impairment. [see Dosage and Administration (2.1) and Use in Specific Populations (8.6)]

Effect of Hepatic Impairment

Anastrozole pharmacokinetics have been investigated in subjects with hepatic cirrhosis related to alcohol abuse. The apparent oral clearance (CL/F) of anastrozole was approximately 30% lower in subjects with stable hepatic cirrhosis than in control subjects with normal liver function. However, these plasma concentrations were still with the range of values observed in normal subjects. The effect of severe hepatic impairment was not studied. No dose adjustment is necessary for stable hepatic cirrhosis. [see Dosage and Administration (2.2) and Use in Specific Populations (8.7)]

NONCLINICAL TOXICOLOGY

13.1 Carcinogenesis, Mutagenesis, Impairment of Fertility

A conventional carcinogenesis study in rats at doses of 1.0 to 25 mg/kg/day (about 10 to 243 times the daily maximum recommended human dose on a mg/m 2 basis) administered by oral gavage for up to 2 years revealed an increase in the incidence of hepatocellular adenoma and carcinoma and uterine stromal polyps in females and thyroid adenoma in males at the high dose. A dose-related increase was observed in the incidence of ovarian and uterine hyperplasia in females. At 25 mg/kg/day, plasma AUC 0-24 hr levels in rats were 110 to 125 times higher than the level exhibited in postmenopausal volunteers at the recommended dose. A separate carcinogenicity study in mice at oral doses of 5 to 50 mg/kg/day (about 24 to 243 times the daily maximum recommended human dose on a mg/m 2 basis) for up to 2 years produced an increase in the incidence of benign ovarian stromal, epithelial and granulosa cell tumors at all dose levels. A dose-related increase in the incidence of ovarian hyperplasia was also observed in female mice. These ovarian changes are considered to be rodent-specific effects of aromatase inhibition and are of questionable significance to humans. The incidence of lymphosarcoma was increased in males and females at the high dose. At 50 mg/kg/day, plasma AUC levels in mice were 35 to 40 times higher than the level exhibited in postmenopausal volunteers at the recommended dose.

Anastrozole has not been shown to be mutagenic in in vitro tests (Ames and E. coli bacterial tests, CHO-K1 gene mutation assay) or clastogenic either in vitro (chromosome aberrations in human lymphocytes) or in vivo (micronucleus test in rats).

Oral administration of anastrozole to female rats (from 2 weeks before mating to pregnancy day 7) produced significant incidence of infertility and reduced numbers of viable pregnancies at 1 mg/kg/day (about 10 times the recommended human dose on a mg/m 2 basis and 9 times higher than the AUC 0-24 hr found in postmenopausal volunteers at the recommended dose). Pre-implantation loss of ova or fetus was increased at doses equal to or greater than 0.02 mg/kg/day (about one-fifth the recommended human dose on a mg/m 2 basis). Recovery of fertility was observed following a 5-week non-dosing period which followed 3 weeks of dosing. It is not known whether these effects observed in female rats are indicative of impaired fertility in humans.

Multiple-dose studies in rats administered anastrozole for 6 months at doses equal to or greater than 1 mg/kg/day (which produced plasma anastrozole C ssmax and AUC 0-24 hr that were 19 and 9 times higher than the respective values found in postmenopausal volunteers at the recommended dose) resulted in hypertrophy of the ovaries and the presence of follicular cysts. In addition, hyperplastic uteri were observed in 6-month studies in female dogs administered doses equal to or greater than 1 mg/kg/day (which produced plasma anastrozole C ssmax and AUC 0-24 hr that were 22 times and 16 times higher than the respective values found in postmenopausal women at the recommended dose). It is not known whether these effects on the reproductive organs of animals are associated with impaired fertility in premenopausal women.

13.2 Animal Toxicology and/or Pharmacology

Reproductive Toxicology

Anastrozole has been found to cross the placenta following oral administration of 0.1 mg/kg in rats and rabbits (about 1 and 1.9 times the recommended human dose, respectively, on a mg/m 2 basis). Studies in both rats and rabbits at doses equal to or greater than 0.1 and 0.02 mg/kg/day, respectively (about 1 and 1/3, respectively, the recommended human dose on a mg/m 2 basis), administered during the period of organogenesis showed that anastrozole increased pregnancy loss (increased pre- and/or post-implantation loss, increased resorption, and decreased numbers of live fetuses); effects were dose related in rats. Placental weights were significantly increased in rats at doses of 0.1 mg/kg/day or more.

Evidence of fetotoxicity, including delayed fetal development (i.e., incomplete ossification and depressed fetal body weights), was observed in rats administered doses of 1 mg/kg/day (which produced plasma anastrozole C ssmax and AUC 0-24 hr that were 19 times and 9 times higher than the respective values found in postmenopausal volunteers at the recommended dose). There was no evidence of teratogenicity in rats administered doses up to 1.0 mg/kg/day. In rabbits, anastrozole caused pregnancy failure at doses equal to or greater than 1.0 mg/kg/day (about 16 times the recommended human dose on a mg/m 2 basis); there was no evidence of teratogenicity in rabbits administered 0.2 mg/kg/day (about 3 times the recommended human dose on a mg/m 2 basis).

PATIENT COUNSELING INFORMATION

“See FDA approved patient labeling (Patient Information).”

17.1 Pregnancy

Patients should be advised that anastrozole may cause fetal harm. They should also be advised that anastrozole is not for use in premenopausal women; therefore, if they become pregnant, they should stop taking anastrozole tablets and immediately contact their doctor.

17.2 Allergic (Hypersensitivity) Reactions

Patients should be informed of the possibility of serious allergic reactions with swelling of the face, lips, tongue and/or throat (angioedema) which may cause difficulty in swallowing and/or breathing and to seek medical attention immediately.

17.3 Ischemic Cardiovascular Events

Patients with pre-existing ischemic heart disease should be informed that an increased incidence of cardiovascular events has been observed with anastrozole use compared to tamoxifen use. If patients have new or worsening chest pain or shortness of breath they should seek medical attention immediately.

17.4 Bone Effects

Patients should be informed that anastrozole lowers the level of estrogen. This may lead to a loss of the mineral content of bones, which might decrease bone strength. A possible consequence of decreased mineral content of bones is an increase in the risk of fractures.

17.5 Cholesterol

Patients should be informed that an increased level of cholesterol might be seen while receiving anastrozole.

17.6 Tickling, Tingling or Numbness

Patients should be informed that if they experience tickling, tingling, or numbness they should notify their health care provider.

17.7 Tamoxifen

Patients should be advised not to take anastrozole with tamoxifen.

17.8 Missed Doses

Inform patients that if they miss a dose, take it as soon as they remember. If it is almost time for their next dose, skip the missed dose and take the next regularly scheduled dose. Patients should not take two doses at the same time.

PATIENT PACKAGE INSERT

Patient Information

Anastrozole Tablets
(an as' troe zole)

What is the most important information I should know about anastrozole tablet? Anastrozole tablets may cause serious side effects including:

heart disease. Women with early breast cancer, who have a history of blockage in their heart arteries (ischemic heart disease) and who take anastrozole tablets, may have an increase in symptoms of decreased blood flow to their heart compared to similar women who take tamoxifen.

Get medical help right away if you have new or worsening chest pain or shortness of breath during treatment with anastrozole tablets.

What is anastrozole tablet?

Anastrozole tablet is a prescription medicine used in women after menopause (“the change of life”) for:

treatment of early breast cancer
after surgery
in women whose breast cancer is hormone receptor-positive

the first treatment of breast cancer that has spread to nearby tissue or lymph nodes (locally advanced) or has spread to other parts of the body (metastatic), in women whose breast cancer is hormone receptor-positive or the hormone receptors are not known

treatment of advanced breast cancer, if the cancer has grown, or the disease has spread after tamoxifen therapy.

Anastrozole tablet does not work in women with breast cancer who have not gone through menopause (premenopausal women).

Who should not take anastrozole tablets?

Do not take anastrozole tablet if you:

are pregnant or able to become pregnant. Anastrozole tablet may harm your unborn baby. If you become pregnant while taking anastrozole tablet, tell your doctor right away.

have not gone through menopause (are premenopausal).
have had a severe allergic reaction to anastrozole or any of the ingredients in anastrozole tablets. See the end of this leaflet for a complete list of ingredients in anastrozole tablets. Symptoms of a severe allergic reaction to
anastrozole tablets include: swelling of the face, lips, tongue or throat, trouble breathing or swallowing, hives and itching.

What should I tell my doctor before taking anastrozole tablets?

Before you take anastrozole tablets, tell your doctor if you:

have not gone through menopause. Talk to your doctor if you are not sure.
have or had a heart problem
have been told you have bone thinning or weakness (osteoporosis)
have high cholesterol
have any other medical conditions

are pregnant or plan to become pregnant. Anastrozole tablet may harm your unborn baby. See “Who should not take anastrozole tablets?”
are breastfeeding or plan to breastfeed. It is not known if anastrozole passes into breast milk. You and your doctor should decide if you will take anastrozole tablets or breastfeed. You should not do both.

Tell your doctor about all the medicines you take, including prescription and over-the-counter medicines, vitamins, and herbal supplements. Especially tell your doctor if you take:

Tamoxifen. You should not take anastrozole tablets if you take tamoxifen. Taking anastrozole tablets with tamoxifen may lower the amount of anastrozole in your blood and may cause anastrozole tablets not to work as well.

Medicines that contain estrogen. Anastrozole tablet may not work if taken with any of these medicines:
hormone replacement therapy
birth control pills
estrogen creams
vaginal rings
vaginal suppositories

Know the medicines you take. Keep a list of them to show your doctor and pharmacist when you get a new medicine.

How should I take anastrozole tablets?

Take anastrozole tablets exactly as your doctor tells you to take it. Continue taking anastrozole tablets until your doctor tells you to stop.

Anastrozole tablets can be taken with or without food.
If you miss a dose, take it as soon as you remember. If it is almost time for your next dose, skip the missed dose. Take your next regularly scheduled dose. Do not take two doses at the same time.
If you take too much anastrozole tablets, call your doctor or go to the nearest hospital emergency room right away.

What are the possible side effects of anastrozole tablets?

Anastrozole tablets may cause serious side effects including:

See “ What is the most important information I should know about anastrozole tablet ?”
bone thinning or weakness (osteoporosis). Anastrozole lowers estrogen in your body, which may cause your bones to become thinner and weaker. This may increase your risk of fractures, especially of your spine, hip and wrist. Your doctor may order a bone mineral density test before you start and during treatment with anastrozole tablets to check you for bone changes.
increased blood cholesterol (fat in the blood). Your doctor may do blood tests to check your cholesterol while you are taking anastrozole tablets.
skin reactions. Stop taking anastrozole tablets and call your doctor right away if you get any skin lesions, ulcers, or blisters.
severe allergic reactions. Get medical help right away if you get:

swelling of your face, lips, tongue, or throat.

trouble swallowing or breathing

liver problems. Anastrozole can cause inflammation of your liver and changes in liver function blood tests. Your doctor may check you for this.
Stop taking anastrozole tablets and call your doctor right away if you have any of these signs or symptoms of a liver problem:

a general feeling of not being well

yellowing of your skin or whites of your eyes

pain on the right side of your stomach-area (abdomen)

Common side effects in women taking anastrozole tablets include:

hot flashes

weakness
joint aches
joint pain, stiffness or swelling (arthritis)

pain

sore throat

high blood pressure

depression

nausea and vomiting

rash

back pain

sleep problems

bone pain

headache

swelling of your legs, ankles, or feet

increased cough

shortness of breath

build up of lymph fluid in the tissues of your affected arm (lymphedema)

Anastrozole tablets may also cause you to have tickling, tingling or numbness of your skin.

Tell your doctor if you have any side effect that bothers you or that does not go away.

These are not all the possible side effects of anastrozole tablets. For more information, ask your doctor or pharmacist.

Call your doctor for medical advice about side effects. You may report side effects to FDA at 1-800-FDA-1088.

How should I store anastrozole tablets?

Store anastrozole tablets at room temperature between 68°F to 77°F (20°C to 25°C).

Keep anastrozole tablets and all medicines out of the reach of children.

General information about the safe and effective use of anastrozole tablets.

Medicines are sometimes prescribed for purposes other than those listed in a Patient Information leaflet. Do not take anastrozole tablets for a condition for which it was not prescribed. Do not give anastrozole tablets to other people, even if they have the same symptoms that you have. It may harm them.

If you would like more information, talk with your doctor. You can ask your pharmacist or doctor for information about anastrozole tablets that is written for health professionals.

What are the ingredients in anastrozole tablets?

Active ingredient: anastrozole

Inactive ingredients: lactose monohydrate, magnesium stearate, hypromellose, macrogol, povidone, sodium starch glycolate, and titanium dioxide.

This Patient Information has been approved by the U.S. Food and Drug Administration.

PACKAGE LABEL.PRINCIPAL DISPLAY PANEL

NDC: 51655-638-53

MFG: 16729-035-15

Anastrozole 1MG

10 Tablets

Rx Only

Lot#

Exp. Date:

Each tablet contains: Anastrozole USP 1mg

Dosage: See prescriber's instructions

Store between 68-77 degrees F. Protect from excessive heat, light and humidity.

Keep out of the reach of children.

Medication guide is found at www.fda.gov/drugs/drugsafety/ucm085729

Manufactured By:

Intas Pharmaceuticals Limited, Ahmedabad – 382 210. India.

Manufactured For:

Accord Healthcare, Inc., Durham, NC 27703

Repackaged by Northwind Pharmaceuticals, Indianapolis, IN 46256